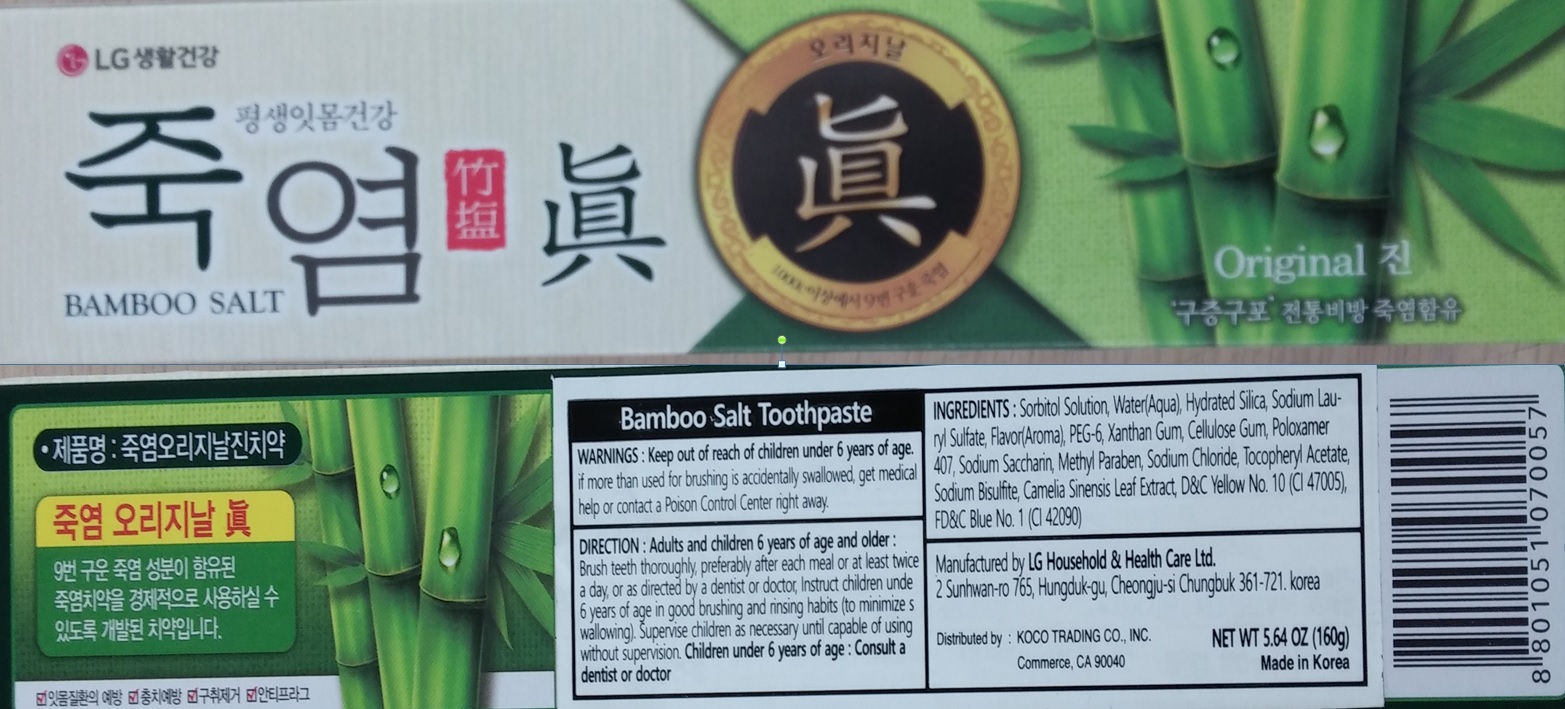 DRUG LABEL: Bamboo Salt 160g
NDC: 69642-1400 | Form: PASTE, DENTIFRICE
Manufacturer: Hanul Trading Co., Ltd.
Category: otc | Type: HUMAN OTC DRUG LABEL
Date: 20170624

ACTIVE INGREDIENTS: SODIUM LAURYL SULFATE 1.21 g/160 g
INACTIVE INGREDIENTS: WATER; XANTHAN GUM

ACTIVE INGREDIENT

Sodium Lauryl Sulfate 0.76%

INACTIVE INGREDIENT

Inactive Ingredient: Sorbitol Solution, Water(Aqua), Hydrated Silica, Flavor(Aroma), PEG-6, Xanthan Gum, Cellulose Gum, Poloxamer 407, Sodium Saccharin, Methyl Paraben, Sodium Chloride, Tocopheryl Acetate, Sodium Bisulfite, Camelia Sinensis Leaf Extract, D&C Yellow NO.10(CI47005), FD&C Blue No.1 (CI 42090)

PURPOSE

Purpose: Oral Health Care

WARNINGS

Warnings: Keep out of reach of children under 6 years of age. If more than used for brushing is accidentally swallowed, get medical help or contact a Poison Control Center right away.

Keep out of reach of children under 6 years of age.

Direction

Direction: Adults and children 6 years of age and older: Brush teeth thoroughly preferably after each meal or at least twice a day, or as directed by a dentist or doctor, Instruct children under 6 years of age in good brushing and rinsing habits (to minimize swallowing). Supervise children as necessary until capable of using without supervision. Children under 6 years of age: Consult a dentist or doctor

Direction

Direction: Adults and children 6 years of age and older: Brush teeth thoroughly preferably after each meal or at least twice a day, or as directed by a dentist or doctor, Instruct children under 6 years of age in good brushing and rinsing habits (to minimize swallowing). Supervise children as necessary until capable of using without supervision. Children under 6 years of age: Consult a dentist or doctor